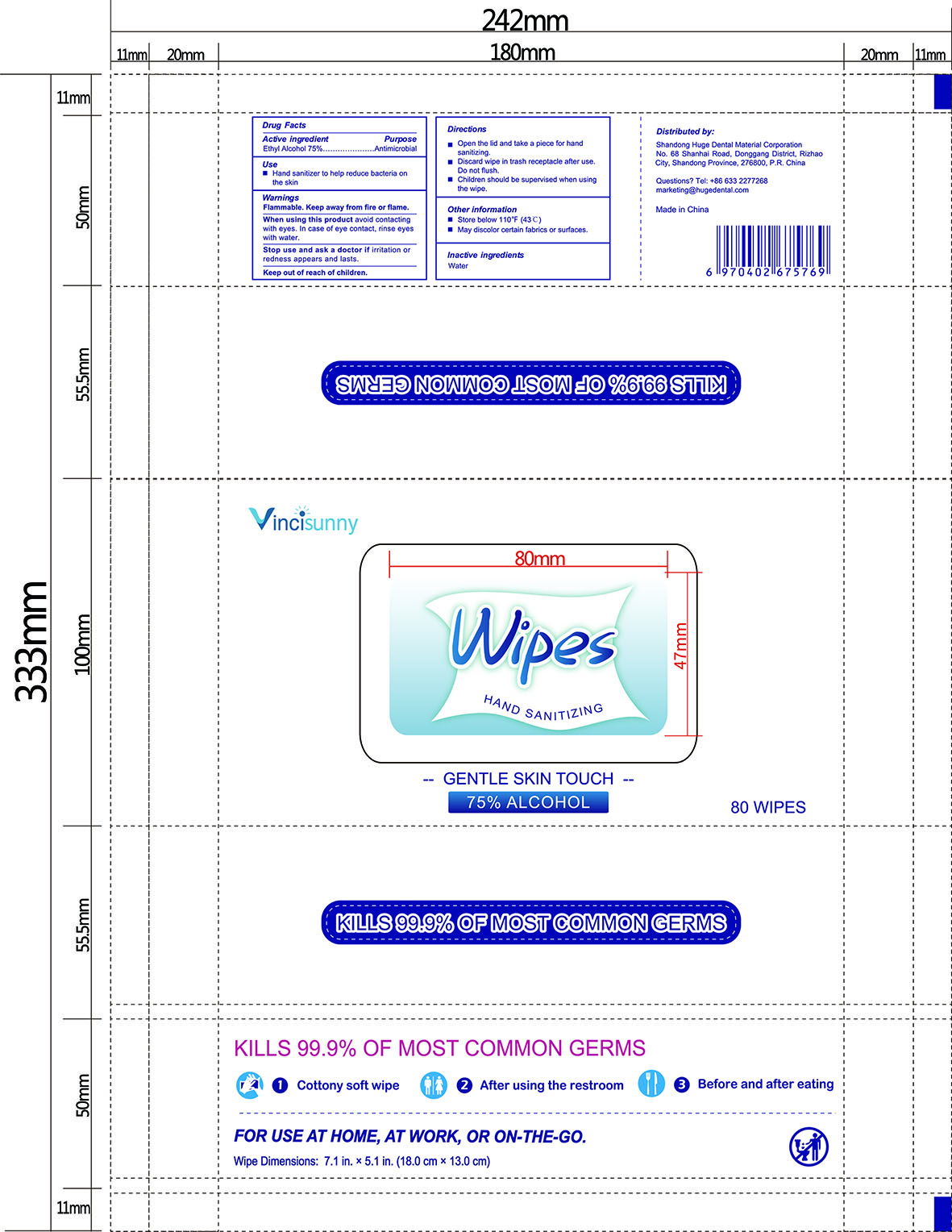 DRUG LABEL: Vincisunny Hand Sanitizing Wipes
NDC: 73718-005 | Form: CLOTH
Manufacturer: Shandong Huge Dental Material Corporation
Category: otc | Type: HUMAN OTC DRUG LABEL
Date: 20200508

ACTIVE INGREDIENTS: ALCOHOL 0.75 mL/1 mL
INACTIVE INGREDIENTS: WATER

Hand Sanitizing Wipes NDC (75% alcohol)

Indications and usage

Hand sanitizer to help reduce bacteria on the skin.

Purpose

Antimicrobial

Active ingredient

Ethyl Alcohol 75%

Inactive ingredients

Water

Dosage and administration

Dosage: CLOTH

Administration: TOPICAL

Warnings

For external use only.
When using this product avoid contacting with eyes. In case of eye contact, rinse eyes with water.
Stop use and ask a doctor if irritation or redness appears and lasts.

Keep out of reach of children. If swallowed, get medical help or contact a Poison Control Center right away.